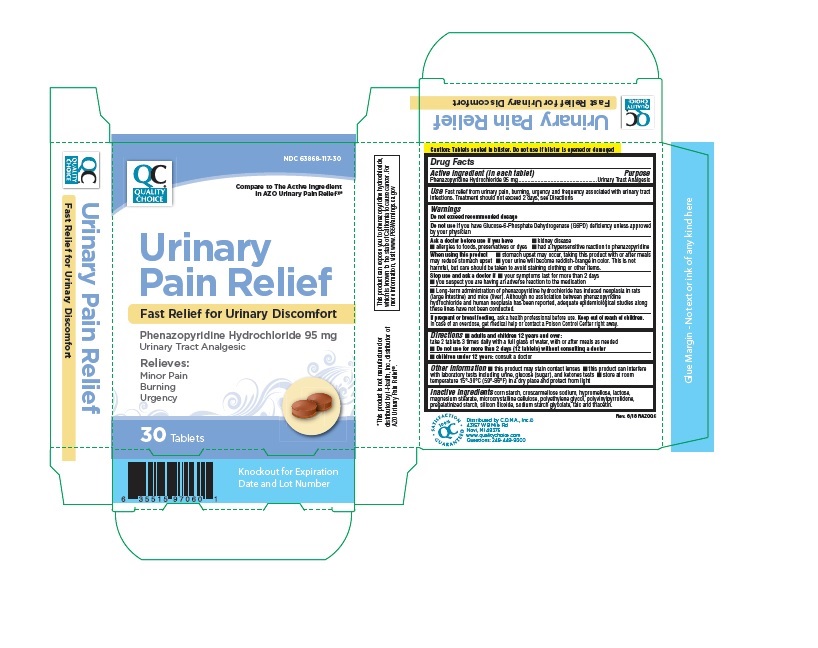 DRUG LABEL: Quality Choice Urinary Pain Relief
                
NDC: 83324-201 | Form: TABLET
Manufacturer: Chain Drug Marketing Association
Category: otc | Type: HUMAN OTC DRUG LABEL
Date: 20251202

ACTIVE INGREDIENTS: PHENAZOPYRIDINE HYDROCHLORIDE 95 mg/1 1
INACTIVE INGREDIENTS: MAGNESIUM STEARATE; CELLULOSE, MICROCRYSTALLINE; SHELLAC; CROSCARMELLOSE SODIUM; SODIUM STARCH GLYCOLATE TYPE A CORN; LACTOSE; MAGNESIUM SILICATE

DRUG FACTS

Active Ingredient

Phenazopyridine Hydrochloride 95 mg

Purpose

Urinary Analgesic

Uses

fast relief from urinary pain,burning,urgency and frequency associated with urinary tract infections.

Warning

Do not exceed recommended dosage

Ask Doctor before use if you have

■ kidney disease
■ allergies to foods, preservatives or dyes
■ had a hypersensitive reaction to Phenazopyridine

■ When using this product stomach upset may occur, taking this product with or after meals may reduce stomach upset
■ your urine will become reddish-orange in color. This is not harmful, but care should be taken to avoid staining clothing or other items.

Stop use and ask a doctor if

■ your symptoms last for more than 2 days
■ you suspect you are having an adverse reaction to the medication

If pregnant or breast feeding

ask a health professional before use.

Keep out of the reach of children

in case of an overdose,get medical help or contact a Poison Control Center right away.

Directions

■ Adults and children 12 and over: take 2 tablets 3 times daily with a full glass of water, with or after meals as needed
■ Children under 12: consult a doctor
■ Do not use for more than 2 days (12 tablets) without consulting a doctor

Inactive Ingredients

lactose, magnesium silicate, magnesium stearate, microcrystalline

cellulose, pharmaceutical glaze, and sodium starch glycolate. May also contain: corn starch,

croscarmellose sodium, polyvinylpyrrolidone, pregelatinized starch and silicon dioxide.